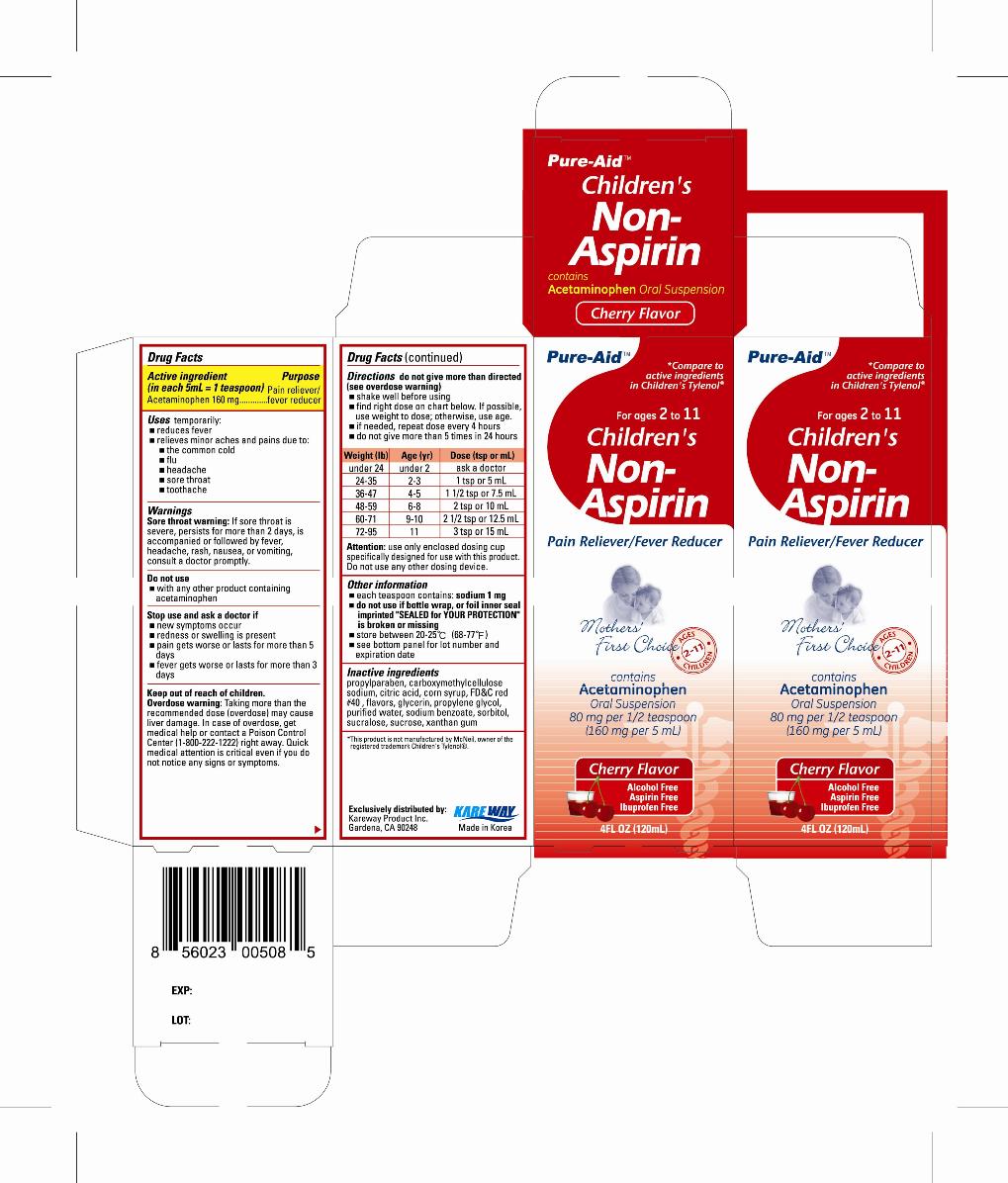 DRUG LABEL: Childrens Non Aspirin
NDC: 67510-0508 | Form: LIQUID
Manufacturer: Kareway Product, Inc.
Category: otc | Type: HUMAN OTC DRUG LABEL
Date: 20110902

ACTIVE INGREDIENTS: ACETAMINOPHEN 160 mg/5 mL
INACTIVE INGREDIENTS: PROPYLPARABEN; CARBOXYMETHYLCELLULOSE SODIUM; CITRIC ACID MONOHYDRATE; CORN SYRUP; FD&C RED NO. 40; GLYCERIN; PROPYLENE GLYCOL; WATER; SODIUM BENZOATE; SORBITOL; SUCRALOSE; SUCROSE; XANTHAN GUM

Drug Facts

Active ingredient (in each 5 ml = 1 teaspoon)

Acetaminophen 160 mg

Purpose

Pain reliever/fever reducer

Uses

temporarily:

- reduces fever
- relieves minor aches and pains due to:
-
  - the common cold
  - flu
  - headache
  - sore throat
  - toothache

Warnings

Sore throat warning: If sore throat is severe, persists for more than 2 days, occurs with or is followed by fever, headache, rash, nausea, or vomiting, consult a doctor promptly.

Do not use

- with any other product containing acetaminophen

Stop use and ask a doctor if

- new symptoms occur
- redness or swelling is present
- pain gets worse or lasts for more than 5 days
- fever gets worse or lasts for more than 3 days

Keep out of reach of children.

Enter section text here

Overdose warning:

Taking more than the recommended dose (overdose) may cause liver damage. In case of overdose, get medical help or contact a Poison Control Center (1-800-222-1222) right away. Quick medical attention is critical even if you do not notice any signs or symptoms.

Directions

do not give more than directed (see overdose warning)

- shake well before using
- find right dose on chart below. If possible use weight to dose; otherwise, use age.
- if needed, repeat dose every 4 hours
- do not give more than 5 times in 24 hours

Weight (lb) | Age (yr) | Dose (tsp or mL)
under 24 | under 2 | ask a doctor
24-35 | 2-3 | 1 tsp or 5 mL
36-47 | 4-5 | 1 1/2 tsp or 7.5 mL
48-59 | 6-8 | 2 tsp or 10 mL
60-71 | 9-10 | 2 1/2 tsp or 12.5 mL
72-95 | 11 | 3 tsp or 15 mL

Attention:use only enclosed dosing cup specifically designed for use with this product. Do not use any other dosing device.

Other information

- each teaspoon contains: sodium 1 mg
- do not use if bottle wrap, or foil inner seal imprinted "SEALED for YOUR PROTECTION" is broken or missing
- store between 20-25°C (68-77°F)
- see bottom panel for lot number and expiration date

Inactive ingredients

propylparaben, carboxymethylcellulose sodium, citric acid, corn syrup, FD and C red #40, flavors, glycerin, propylene glycol, purified water, sodium benzoate, sorbitol, sucralose, sucrose, xanthan gum

Package label

Children's Non-Aspirin